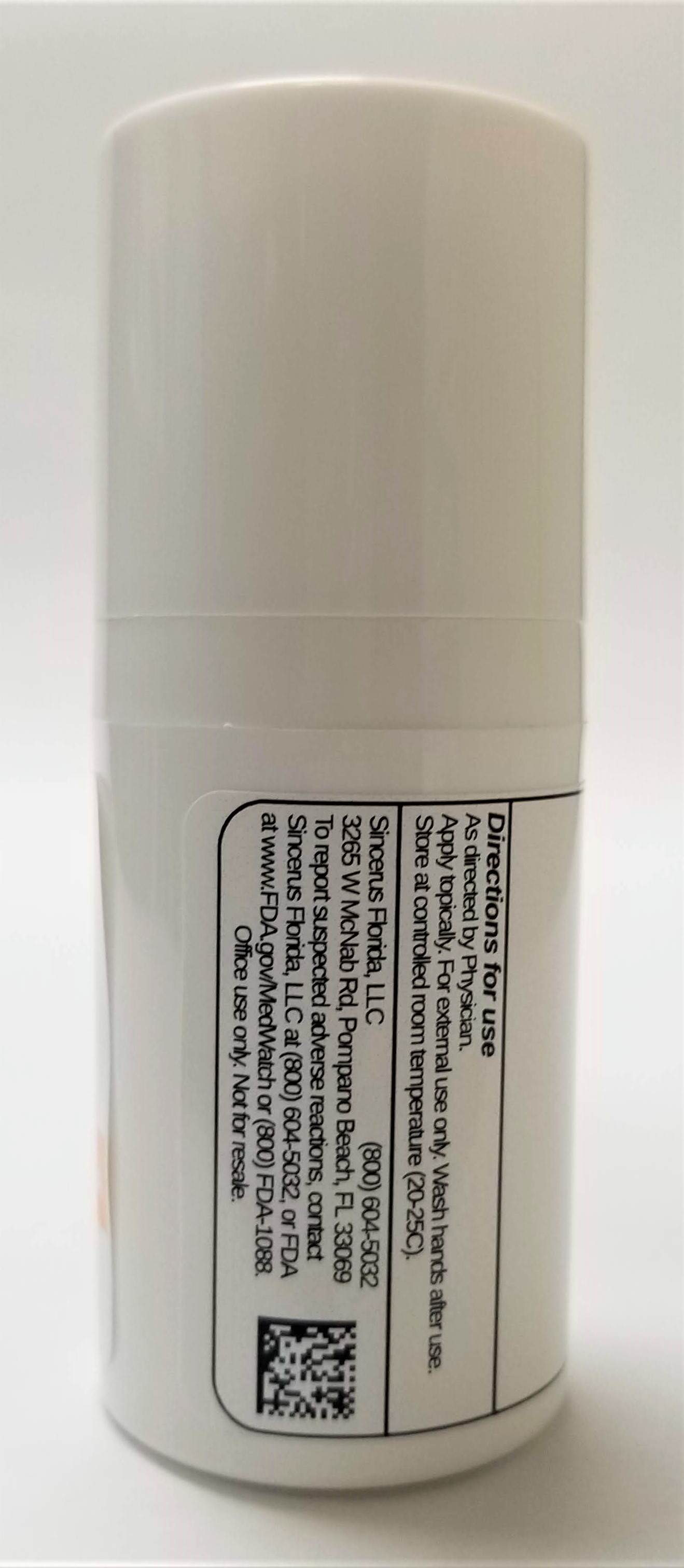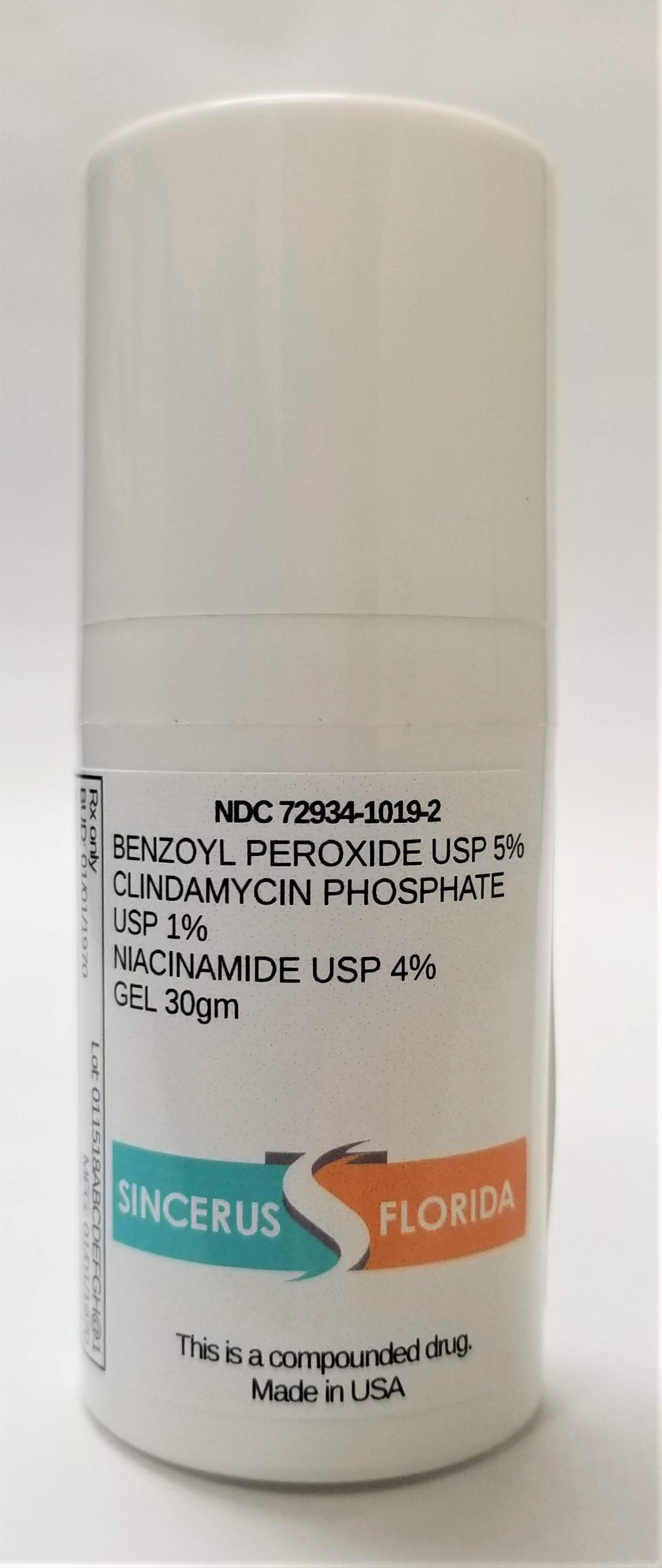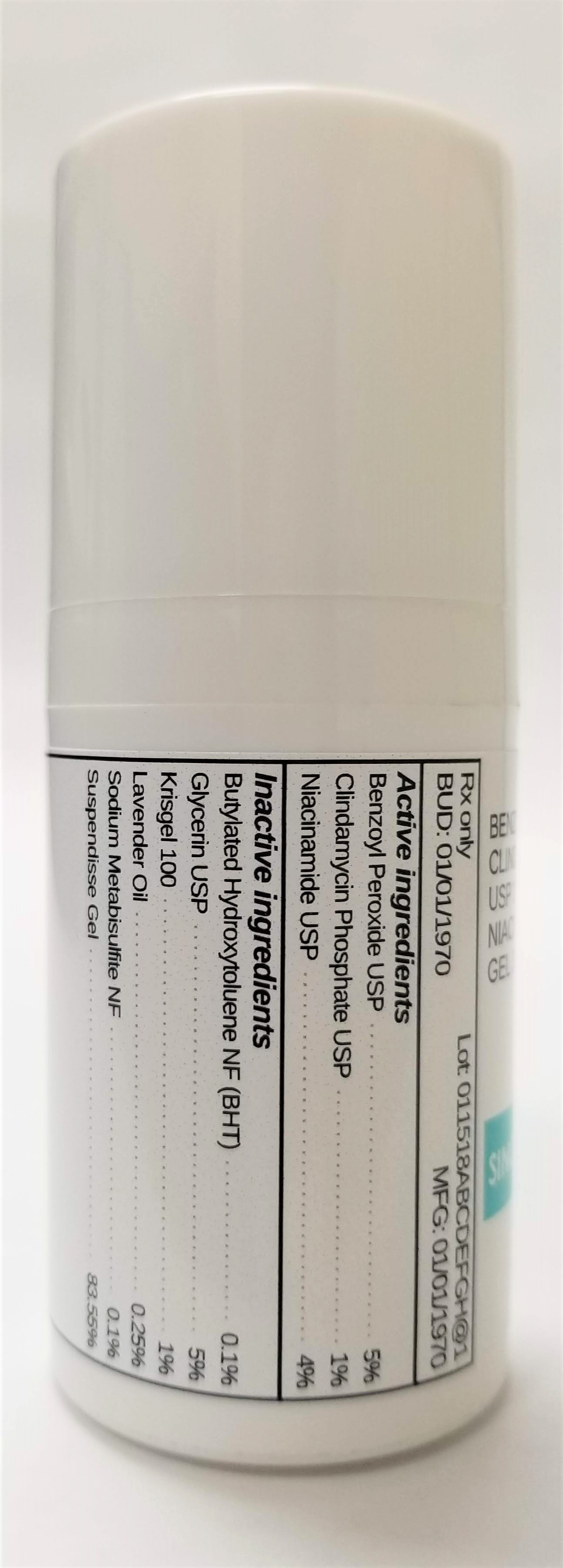 DRUG LABEL: BENZOYL PEROXIDE 5% / CLINDAMYCIN 1% / NIACINAMIDE 4%
NDC: 72934-1019 | Form: GEL
Manufacturer: Sincerus Florida, LLC
Category: prescription | Type: HUMAN PRESCRIPTION DRUG LABEL
Date: 20190423

ACTIVE INGREDIENTS: BENZOYL PEROXIDE 5 g/100 g; CLINDAMYCIN PHOSPHATE 1 g/100 g; NIACINAMIDE 4 g/100 g

BENZOYL PEROXIDE 5% / CLINDAMYCIN 1% / NIACINAMIDE 4%